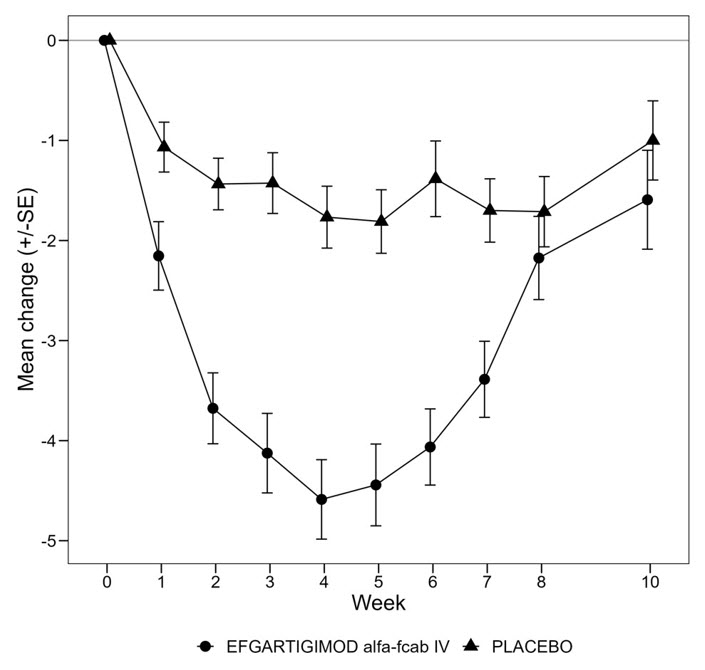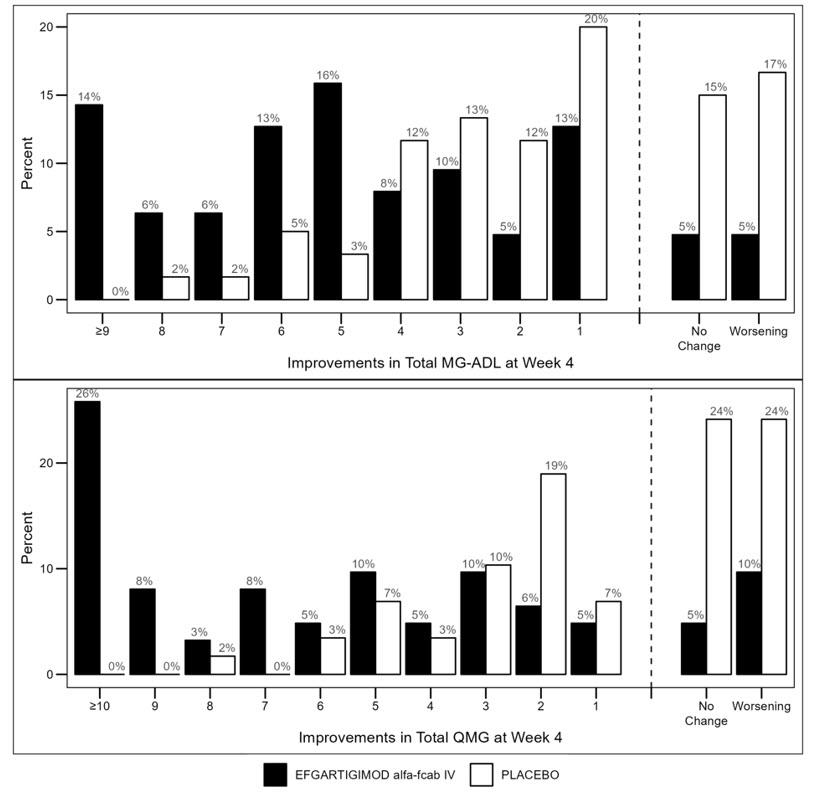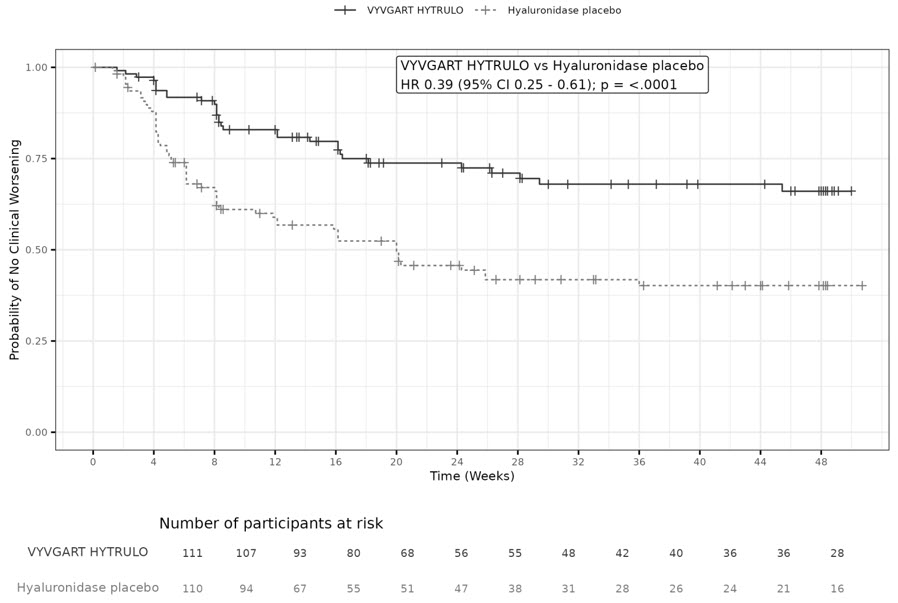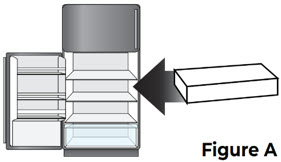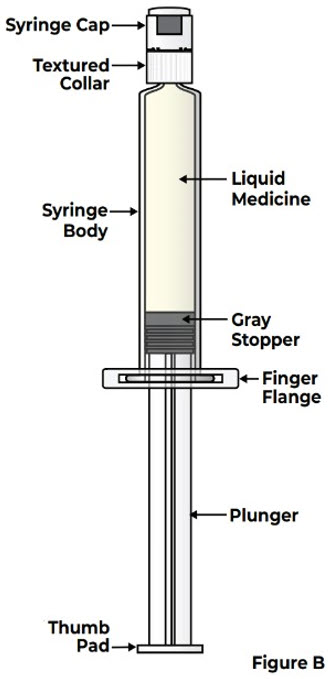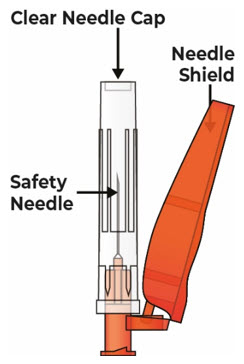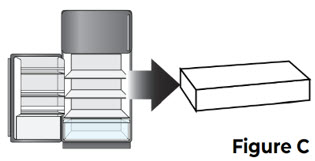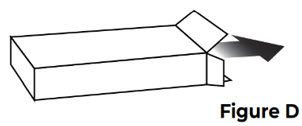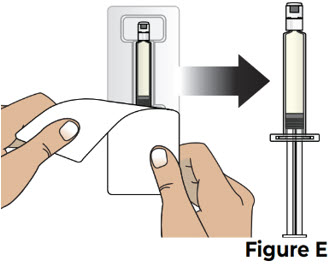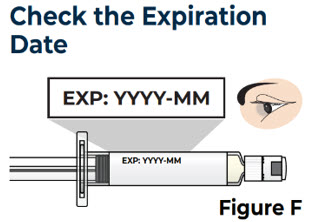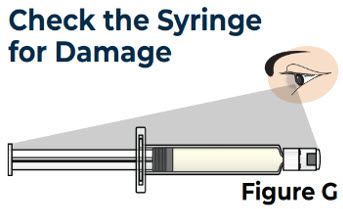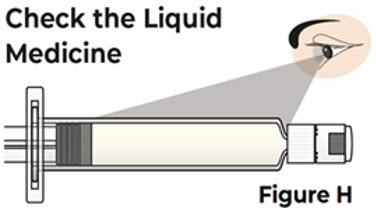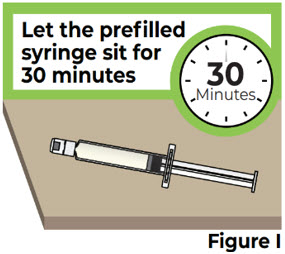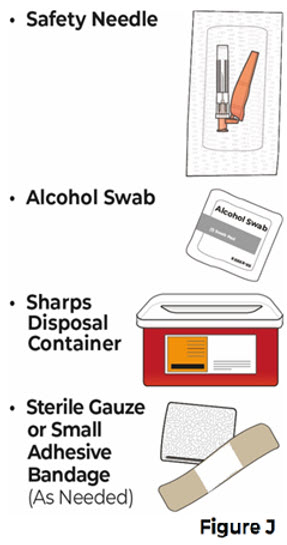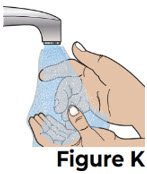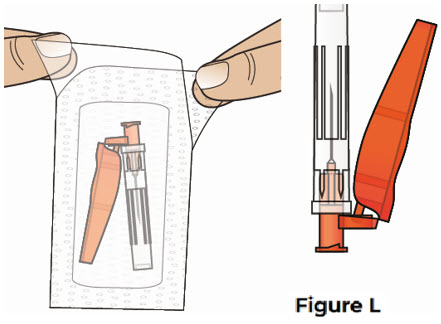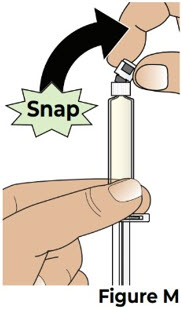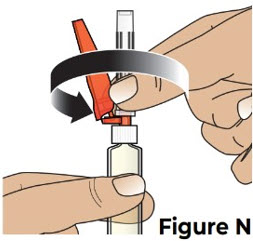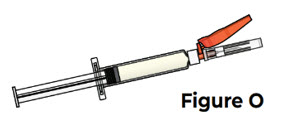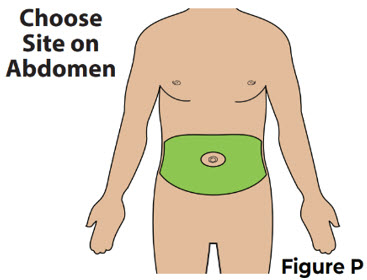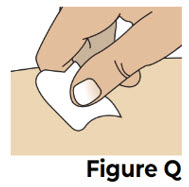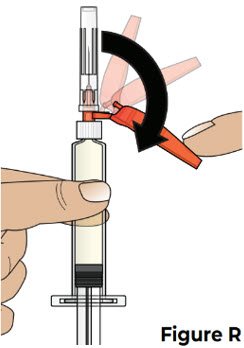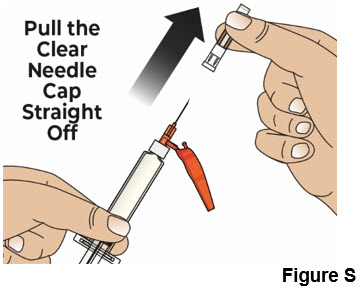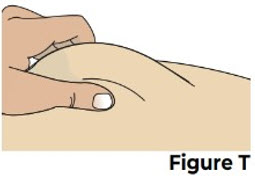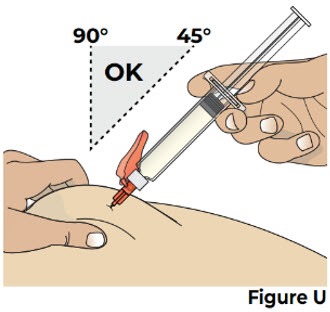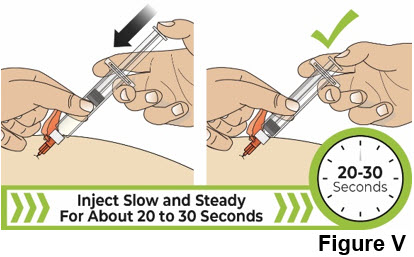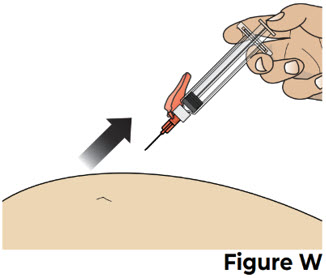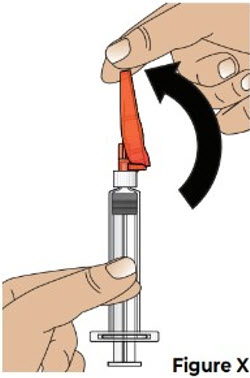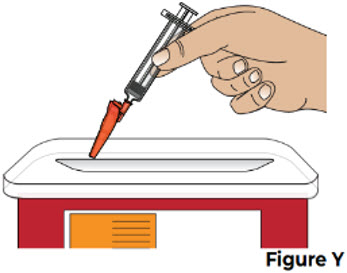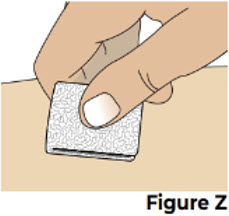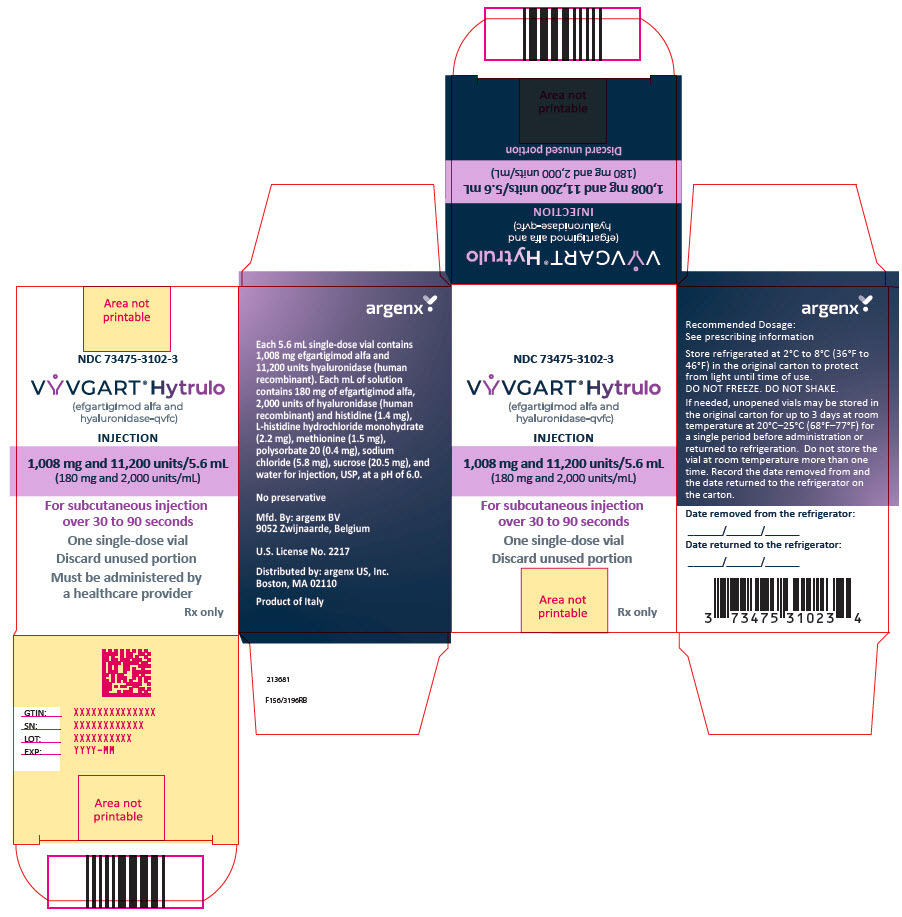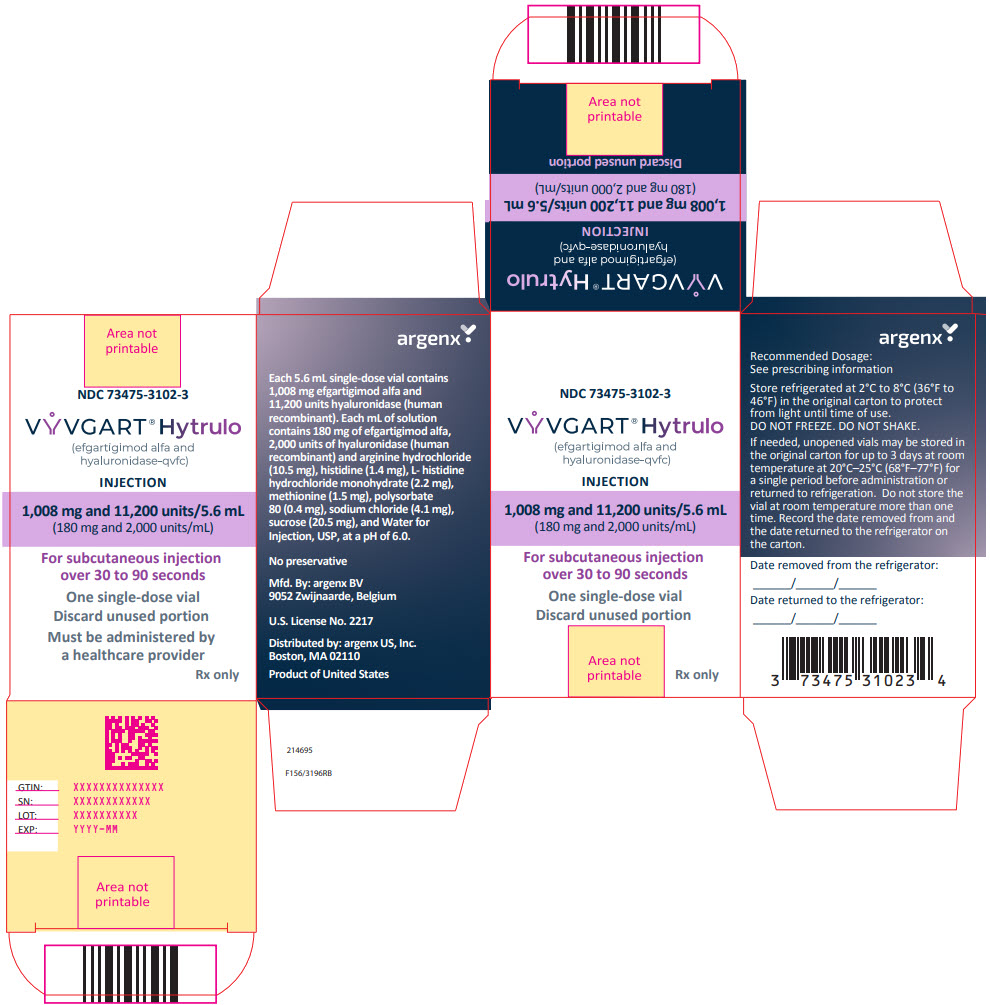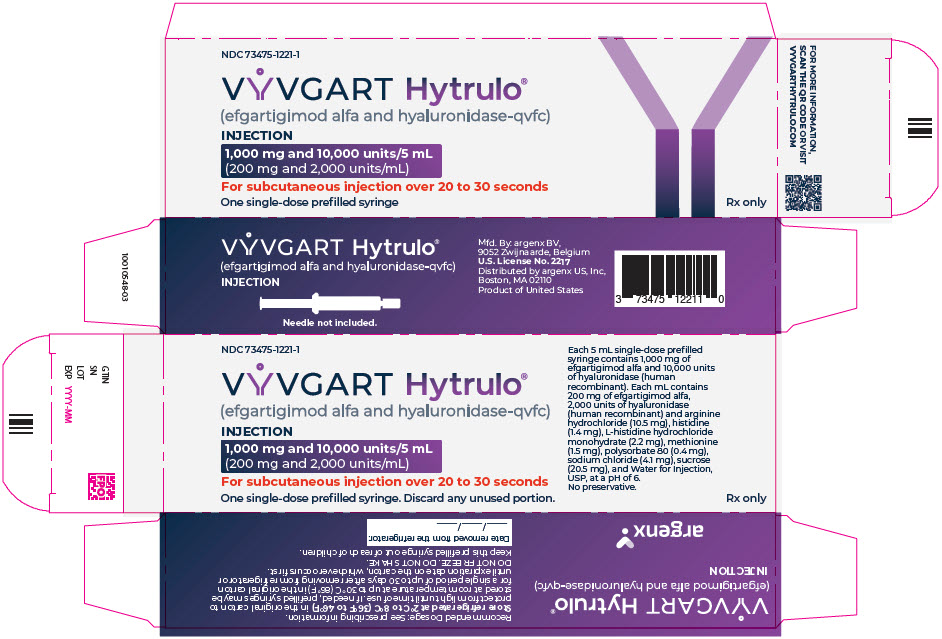 DRUG LABEL: VYVGART Hytrulo
NDC: 73475-3102 | Form: INJECTION, SOLUTION
Manufacturer: argenx US
Category: prescription | Type: HUMAN PRESCRIPTION DRUG LABEL
Date: 20260213

ACTIVE INGREDIENTS: EFGARTIGIMOD ALFA 180 mg/1 mL; HYALURONIDASE (HUMAN RECOMBINANT) 2000 U/1 mL
INACTIVE INGREDIENTS: histidine; HISTIDINE MONOHYDROCHLORIDE; methionine; polysorbate 20; sodium chloride; sucrose; WATER

HIGHLIGHTS OF PRESCRIBING INFORMATION

These highlights do not include all the information needed to use VYVGART HYTRULO safely and effectively. See full prescribing information for VYVGART HYTRULO.
VYVGART HYTRULO® (efgartigimod alfa and hyaluronidase-qvfc) injection, for subcutaneous use
Initial U.S. Approval: 2023

RECENT MAJOR CHANGES

Dosage and Administration (2.3) | 10/2025
Dosage and Administration (2.2, 2.5) | 4/2025
Dosage and Administration (2.4) | 2/2026

1 INDICATIONS AND USAGE

VYVGART HYTRULO is a combination of efgartigimod alfa, a neonatal Fc receptor blocker, and hyaluronidase, an endoglycosidase, indicated for the treatment of adult patients with:

- generalized myasthenia gravis (gMG) who are anti-acetylcholine receptor (AChR) antibody positive (1)
- chronic inflammatory demyelinating polyneuropathy (CIDP) (1)

2 DOSAGE AND ADMINISTRATION

- See Full Prescribing Information for instructions on dosage, preparation, and administration. (2.1, 2.2, 2.3, 2.4, 2.5)
- Evaluate the need to administer age-appropriate vaccines according to immunization guidelines before initiation of a new treatment cycle with VYVGART HYTRULO. (2.1)
- Important Administration Information
  - VYVGART HYTRULO is for subcutaneous use only. (2.2)
  - Prefilled syringe can be administered by patients and/or caregivers. (2.2)
  - Vial to be administered with a winged infusion set by a healthcare professional only. (2.2)
- gMG: recommended dose and dose schedule
  - Administer in cycles of once weekly injections for 4 weeks. (2.3)
  - Prefilled syringe: 1,000 mg efgartigimod alfa and 10,000 units hyaluronidase administered over 20 to 30 seconds. (2.3)
  - Vial: 1,008 mg efgartigimod alfa and 11,200 units hyaluronidase over 30 to 90 seconds. (2.3)
  - Administer subsequent treatment cycles based on clinical evaluation. (2.3)
- CIDP: recommended dose and dose schedule
  - Administer as once weekly injections. (2.4)
  - Prefilled syringe: 1,000 mg efgartigimod alfa and 10,000 units hyaluronidase administered over approximately 20 to 30 seconds. (2.4)
  - Vial: 1,008 mg efgartigimod alfa and 11,200 units hyaluronidase over 30 to 90 seconds. (2.4)

3 DOSAGE FORMS AND STRENGTHS

Injection: 1,000 mg efgartigimod alfa and 10,000 units hyaluronidase per 5 mL (200 mg/2,000 units per mL) in a single-dose prefilled syringe. (3)

Injection: 1,008 mg efgartigimod alfa and 11,200 units hyaluronidase per 5.6 mL (180 mg/2,000 units per mL) in a single-dose vial. (3)

4 CONTRAINDICATIONS

VYVGART HYTRULO is contraindicated in patients with serious hypersensitivity to efgartigimod alfa products, to hyaluronidase, or to any of the excipients of VYVGART HYTRULO. (4)

5 WARNINGS AND PRECAUTIONS

- Infections: Delay administration of VYVGART HYTRULO to patients with an active infection. Monitor for signs and symptoms of infection in patients treated with VYVGART HYTRULO. If serious infection occurs, administer appropriate treatment and consider withholding VYVGART HYTRULO until the infection has resolved. (5.1)
- Hypersensitivity Reactions: Anaphylaxis, hypotension leading to syncope, angioedema, dyspnea, rash, and urticaria have occurred in patients treated with VYVGART HYTRULO or intravenous efgartigimod alfa-fcab product. If a hypersensitivity reaction occurs, the healthcare professional should institute appropriate measures if needed or the patient should seek medical attention. (4, 5.2)
- Infusion/injection-Related Reactions: If a severe infusion/injection-related reaction occurs, initiate appropriate therapy; consider the risks and benefits of readministering. If a mild to moderate infusion/injection-related reaction occurs, may rechallenge with close clinical observation, slower infusion/injection rates, and pre-medications. (5.3)

6 ADVERSE REACTIONS

The most common adverse reactions (≥ 10%) in patients with gMG treated with efgartigimod alfa-fcab were respiratory tract infections, headache, and urinary tract infection.

Injection site reactions were common (≥ 15%) in patients with gMG and CIDP who were treated with VYVGART HYTRULO (6.1)

To report SUSPECTED ADVERSE REACTIONS, contact argenx at 1-833-argx411 or FDA at 1-800-FDA-1088 or www.fda.gov/medwatch.

7 DRUG INTERACTIONS

Closely monitor for reduced effectiveness of medications that bind to the human neonatal Fc receptor. When concomitant long-term use of such medications is essential for patient care, consider discontinuing VYVGART HYTRULO and using alternative therapies. (7)

FULL PRESCRIBING INFORMATION

1 INDICATIONS AND USAGE

VYVGART HYTRULO is indicated for the treatment of adult patients with:

- generalized myasthenia gravis (gMG) who are anti-acetylcholine receptor (AChR) antibody positive
- chronic inflammatory demyelinating polyneuropathy (CIDP)

2 DOSAGE AND ADMINISTRATION

2.1 Recommended Vaccination

Evaluate the need to administer age-appropriate vaccines according to immunization guidelines before initiation of a new treatment cycle with VYVGART HYTRULO. Because VYVGART HYTRULO causes transient reduction in IgG levels, vaccination with live vaccines is not recommended during treatment with VYVGART HYTRULO [see Dosage and Administration (2.3) and Warnings and Precautions (5.1)].

2.2 Important Dosage and Administration Instructions

VYVGART HYTRULO is for subcutaneous use only. Do not administer intravenously. Do not dilute VYVGART HYTRULO.

Single-Dose Prefilled Syringe

VYVGART HYTRULO prefilled syringe may be administered by patients and/or caregivers after proper instruction in subcutaneous injection technique [see Instructions for Use].

Single-Dose Vial

VYVGART HYTRULO vial is to be administered with a winged infusion set by a healthcare professional only [see Dosage and Administration (2.4)].

2.3 Recommended Dosage for gMG

Single-Dose Prefilled Syringe

The recommended dosage of VYVGART HYTRULO prefilled syringe is 1,000 mg / 10,000 units (1,000 mg efgartigimod alfa and 10,000 units hyaluronidase) administered subcutaneously over approximately 20 to 30 seconds in cycles of once weekly injections for 4 weeks.

Single-Dose Vial

The recommended dosage of VYVGART HYTRULO vial is 1,008 mg / 11,200 units (1,008 mg efgartigimod alfa and 11,200 units hyaluronidase) administered subcutaneously over approximately 30 to 90 seconds in cycles of once weekly injections for 4 weeks.

General Dosage Considerations

Administer subsequent treatment cycles according to clinical evaluation.

If a scheduled dose is missed, VYVGART HYTRULO may be administered up to 3 days after the scheduled time point. Thereafter, resume the original dosing schedule until the treatment cycle is completed.

2.4 Recommended Dosage for CIDP

Single-Dose Prefilled Syringe

The recommended dosage of VYVGART HYTRULO prefilled syringe is 1,000 mg / 10,000 units (1,000 mg efgartigimod alfa and 10,000 units hyaluronidase) administered subcutaneously over approximately 20 to 30 seconds as once weekly injections.

Single-Dose Vial

The recommended dosage of VYVGART HYTRULO vial is 1,008 mg / 11,200 units (1,008 mg efgartigimod alfa and 11,200 units hyaluronidase) administered subcutaneously over approximately 30 to 90 seconds as once weekly injections.

General Dosage Considerations

If a scheduled injection is missed, VYVGART HYTRULO may be administered up to 3 days after the scheduled time point. Thereafter, resume the original dosing schedule.

Not all patients respond to VYVGART HYTRULO. Consider the appropriateness of continuing treatment in patients who experience worsening of neurological symptoms after starting VYVGART HYTRULO [see Adverse Reactions (6.2) and Clinical Studies (14.2)].

2.5 Preparation and Administration Instructions

Single-Dose Prefilled Syringe

- Take the VYVGART HYTRULO prefilled syringe out of the refrigerator at least 30 minutes before injecting to allow it to reach room temperature [see How Supplied/Storage and Handling (16)]. Do not use external heat sources to bring the syringe to room temperature.
- Parenteral drug products should be inspected visually for particulate matter and discoloration prior to administration, whenever solution and container permit. Visually inspect that the prefilled syringe solution is yellowish, clear to opalescent and devoid of particulate matter. Do not use if visible particles are present.
- Each prefilled syringe is for one-time use only.
- To administer VYVGART HYTRULO prefilled syringe, use a safety needle that is 25G, 5/8 inches in length, and thin wall type. The safety needle is not included in the carton.
- Choose an injection site on the abdomen (at least 2 inches away from the navel).
  - Do not inject on areas where the skin is irritated, red, bruised, infected, tender, hard, or into areas where there are moles or scars.
  - Rotate injection sites for subsequent administrations.
- Inject VYVGART HYTRULO prefilled syringe subcutaneously into a pinched skin area at an angle of 45 to 90 degrees for approximately 20 to 30 seconds.
- Discard any unused portions of medicine remaining in the syringe.
- Localized injection site reactions may occur after VYVGART HYTRULO is administered [see Adverse Reactions (6.1)].
- Monitor for clinical signs and symptoms of hypersensitivity reactions for at least 30 minutes after administration. If a hypersensitivity reaction occurs, the patient should seek medical attention and the healthcare professional should institute appropriate measures, if needed [see Warnings and Precautions (5.2)].

For detailed instructions on the preparation and administration of VYVGART HYTRULO prefilled syringe see INSTRUCTIONS FOR USE.

Single-Dose Vial

Use aseptic technique when preparing and administering VYVGART HYTRULO vial. Do not shake the vial. Each vial is for one-time use only. Avoid exposure to direct sunlight.

Preparation

- Take the VYVGART HYTRULO vial out of the refrigerator at least 15 minutes before injecting to allow it to reach room temperature [see How Supplied/Storage and Handling (16)]. Do not use external heat sources.
- Check that the VYVGART HYTRULO solution is yellowish, clear to opalescent.
- Parenteral medicine products should be inspected visually for particulate matter prior to administration, whenever solution and container permit. Do not use if opaque particles or other foreign particles are present.
- Withdraw the entire content of VYVGART HYTRULO from the vial using a polypropylene syringe and an 18G stainless steel transfer needle.
- Remove large air bubbles, if present.
- Each vial contains overfill to compensate for liquid loss during preparation and to compensate for the priming volume of the winged infusion set.
- VYVGART HYTRULO vial does not contain preservatives. Administer immediately after preparation.

Administration

- To administer VYVGART HYTRULO vial use a winged infusion set made of polyvinyl chloride (PVC), 25G, 12 inches tubing, maximum priming volume of 0.4 mL.
- Remove the transfer needle from the syringe and connect the syringe to the winged infusion set.
- Prior to administration, fill the tubing of the winged infusion set by gently pressing the syringe plunger until the plunger is at 5.6 mL. There should be solution at the end of the winged infusion set needle.
- Choose an injection site on the abdomen (at least 2 to 3 inches away from the navel).
  - Do not inject on areas where the skin is red, bruised, tender, hard, or into areas where there are moles or scars.
  - Rotate injection sites for subsequent administrations.
- Inject VYVGART HYTRULO vial subcutaneously into a pinched skin area at an angle of about 45 degrees over 30 to 90 seconds.
- Localized injection site reactions may occur after VYVGART HYTRULO is administered. [see Adverse Reactions (6.1)].
- Discard any unused portions of medicine remaining in the vial, the syringe and the winged infusion set.
- Healthcare professionals should monitor for clinical signs and symptoms of hypersensitivity reactions for at least 30 minutes after administration. If a hypersensitivity reaction occurs, the healthcare professional should institute appropriate measures if needed or the patient should seek medical attention [see Warnings and Precautions (5.2)].

3 DOSAGE FORMS AND STRENGTHS

Injection: 1,000 mg efgartigimod alfa and 10,000 units hyaluronidase per 5 mL (200 mg/2,000 units per mL) as yellowish, clear to opalescent solution, in a single-dose prefilled syringe.

Injection: 1,008 mg efgartigimod alfa and 11,200 units hyaluronidase per 5.6 mL (180 mg/2,000 units per mL) as yellowish, clear to opalescent solution, in a single-dose vial.

4 CONTRAINDICATIONS

VYVGART HYTRULO is contraindicated in patients with serious hypersensitivity to efgartigimod alfa products, to hyaluronidase, or to any of the excipients of VYVGART HYTRULO. Reactions have included anaphylaxis and hypotension leading to syncope [see Warnings and Precautions (5.2)].

5 WARNINGS AND PRECAUTIONS

5.1 Infections

VYVGART HYTRULO may increase the risk of infection. The most common infections observed in Study 1 were urinary tract infection (10% of efgartigimod alfa-fcab-treated patients compared to 5% of placebo-treated patients) and respiratory tract infections (33% of efgartigimod alfa-fcab- treated patients compared to 29% of placebo-treated patients) [see Adverse Reactions (6.1) and Clinical Studies (14)]. A higher frequency of patients who received efgartigimod alfa-fcab compared to placebo were observed to have below normal levels for white blood cell counts (12% versus 5%, respectively), lymphocyte counts (28% versus 19%, respectively), and neutrophil counts (13% versus 6%, respectively). The majority of infections and hematologic abnormalities were mild to moderate in severity. Delay VYVGART HYTRULO administration in patients with an active infection until the infection is resolved. During treatment with VYVGART HYTRULO, monitor for clinical signs and symptoms of infections. If serious infection occurs, administer appropriate treatment and consider withholding VYVGART HYTRULO until the infection has resolved.

Immunization

Evaluate the need to administer age-appropriate vaccines according to immunization guidelines before initiation of a new treatment cycle with VYVGART HYTRULO. The safety of immunization with live vaccines and the immune response to vaccination during treatment with VYVGART HYTRULO are unknown. Because VYVGART HYTRULO causes a reduction in IgG levels, vaccination with live vaccines is not recommended during treatment with VYVGART HYTRULO.

5.2 Hypersensitivity Reactions

In clinical trials, hypersensitivity reactions, including rash, angioedema, and dyspnea were observed in patients treated with VYVGART HYTRULO or intravenous efgartigimod alfa-fcab. Urticaria was also observed in patients treated with VYVGART HYTRULO. Hypersensitivity reactions were mild or moderate, occurred within one hour to three weeks of administration.

Anaphylaxis and hypotension leading to syncope have been reported in postmarketing experience with intravenous efgartigimod alfa-fcab. Anaphylaxis and hypotension occurred during or within an hour of administration and led to infusion discontinuation and in some cases to permanent treatment discontinuation.

Monitor for clinical signs and symptoms of hypersensitivity reactions for at least 30 minutes after administration [see Dosage and Administration (2.4)]. If a hypersensitivity reaction occurs, the healthcare professional should institute appropriate measures if needed or the patient should seek medical attention. VYVGART HYTRULO is contraindicated in patients with a history of serious hypersensitivity to efgartigimod alfa products, to hyaluronidase, or to any of the excipients of VYVGART HYTRULO [see Contraindications (4)].

5.3 Infusion/Injection-Related Reactions

Infusion-related reactions have been reported with intravenous efgartigimod alfa-fcab in postmarketing experience. The most frequent symptoms and signs were hypertension, chills, shivering, and thoracic, abdominal, and back pain. Infusion-related reactions occurred during or within an hour of administration and led to infusion discontinuation. If a severe infusion/injection-related reaction occurs, initiate appropriate therapy. Consider the risks and benefits of readministering VYVGART HYTRULO following a severe infusion/injection-related reaction. If a mild to moderate infusion/injection-related reaction occurs, patients may be rechallenged with close clinical observation, slower infusion/injection rates, and pre-medications.

6 ADVERSE REACTIONS

The following clinically significant adverse reactions are described elsewhere in the labeling:

- Infections [see Warnings and Precautions (5.1)]
- Hypersensitivity Reactions [see Warnings and Precautions (5.2)]
- Infusion/Injection-Related Reactions [see Warnings and Precautions (5.3)]

6.1 Clinical Trials Experience

Because clinical trials are conducted under widely varying conditions, adverse reaction rates observed in the clinical trials of a drug cannot be directly compared to rates in the clinical trials of another drug and may not reflect the rates observed in practice.

Clinical Experience in Patients with gMG

The safety of efgartigimod alfa in patients with gMG was established in a double blinded placebo-controlled study with efgartigimod alfa-fcab administered intravenously (Study 1) and its open-label extension, and in an active-controlled study of VYVGART HYTRULO administered subcutaneously (Study 2) and its open-label extension [see Clinical Studies (14.1)].

Adverse Reactions with Efgartigimod Alfa-fcab Intravenous in Patients with gMG

In clinical studies, the safety of efgartigimod alfa-fcab administered intravenously has been evaluated in 246 patients with gMG who received at least one dose of efgartigimod alfa-fcab, including 57 patients exposed to at least 7 treatment cycles and 8 patients exposed to at least 10 treatment cycles.

In a placebo-controlled study (Study 1) in patients with gMG, 84 patients received efgartigimod alfa-fcab 10 mg/kg [see Clinical Studies (14)]. Of these 84 patients, approximately 75% were female, 82% were White, 11% were Asian, and 8% were of Hispanic or Latino ethnicity. The mean age at study entry was 46 years (range 19 to 78).

The minimum time to initiate a subsequent cycle, specified by study protocol, was 28 days from the last administration of the previous treatment cycle. On average, efgartigimod alfa-fcab-treated patients received 2 cycles in Study 1. The mean and median times to the second treatment cycle were 54 days and 50 days from the last administration of the first treatment cycle, respectively, for efgartigimod alfa-fcab-treated patients.

Adverse reactions reported in at least 5% of patients treated with efgartigimod alfa-fcab and more frequently than placebo are summarized in Table 1. The most common adverse reactions (reported in at least 10% of efgartigimod alfa-fcab-treated patients) were respiratory tract infection, headache, and urinary tract infection.

Table 1: Adverse Reactions in at least 5% of Patients with gMG Treated with Efgartigimod Alfa-fcab Intravenously (EFG IV) and More Frequently than in Placebo-Treated Patients in Study 1 (Safety Population)
Adverse reaction | EFG IV (N=84) % | Placebo (N=83) %
Respiratory tract infection | 33 | 29
Headache [Headache includes migraine and procedural headache.] | 32 | 29
Urinary tract infection | 10 | 5
Paraesthesia [Paresthesia includes oral hypoesthesia, hypoesthesia, and hyperesthesia.] | 7 | 5
Myalgia | 6 | 1

The safety of initiating subsequent cycles between 7 and 28 days from the last administration of the previous treatment cycle was assessed in 60 patients. Of these patients, 63% were exposed to treatment for over a year when cycles were initiated less than 4 weeks after the last administration. Safety in these patients was similar to that seen in Study 1.

Adverse Reactions with VYVGART HYTRULO in Patients with gMG

In an active-controlled study in patients with gMG (Study 2), 110 patients were randomized and received one cycle of once weekly administrations for 4 weeks (4 administrations total), of either VYVGART HYTRULO subcutaneously (n=55) or efgartigimod alfa-fcab intravenously (n=55) at recommended doses [see Dosage and Administration (2.2)]. The open-label extension of Study 2 included some patients who switched from efgartigimod alfa-fcab IV to VYVGART HYTRULO.

The most common adverse reactions (reported in at least 10% of VYVGART HYTRULO-treated patients) were injection site reactions and headache.

In Study 2, injection site reactions occurred in 38% of patients receiving VYVGART HYTRULO. These were injection site rash, erythema, pruritus, bruising, pain, and urticaria.

In Study 2 and its open-label extension (n = 168), all injection site reactions were mild to moderate in severity and did not lead to treatment discontinuation. The majority occurred within 24 hours after administration and resolved spontaneously. Most injection site reactions occurred during the first treatment cycle, and the incidence decreased with each subsequent cycle.

Clinical Experience in Patients with CIDP

Adverse Reactions with VYVGART HYTRULO in Patients with CIDP

In a placebo-controlled study in patients with CIDP (Study 3, stage B), 221 patients were randomized to receive once-weekly administration of either VYVGART HYTRULO 1,008 mg /11, 200 units subcutaneously (n=111) or placebo (n=110) [see Clinical Studies (14.2)]. The mean duration of treatment with VYVGART HYTRULO in stage B was 25 weeks. The overall safety profile observed in patients with CIDP treated with VYVGART HYTRULO was consistent with the known safety profile of VYVGART HYTRULO and of efgartigimod alfa-fcab administered intravenously.

In Study 3, injection site reactions occurred in 15% of patients treated with VYVGART HYTRULO compared to 6% of patients who received placebo. The most common of these injection site reactions were injection site bruising and injection site erythema. All injection site reactions were mild to moderate in severity. Most injection site reactions occurred during the first 3 months of treatment.

6.2 Postmarketing Experience

The following adverse reactions have been identified during postapproval use of efgartigimod alfa products. Because these reactions are reported voluntarily from a population of uncertain size, it is not always possible to reliably estimate their frequency or establish a causal relationship to drug exposure.

Immune System Disorders: Hypersensitivity reactions including anaphylaxis and hypotension, and infusion/injection-related reactions [see Warnings and Precautions (5.2, 5.3)].

Neurological: There have been reports of worsening of symptoms and signs of CIDP when transitioning from intravenous immunoglobulin treatments to VYVGART HYTRULO [see Drug Interactions (7.1)].

7 DRUG INTERACTIONS

7.1 Effect of VYVGART HYTRULO on Other Drugs

Concomitant use of VYVGART HYTRULO with medications that bind to the human neonatal Fc receptor (FcRn) (e.g., immunoglobulin products, monoclonal antibodies, or antibody derivates containing the human Fc domain of the IgG subclass) may lower systemic exposures and reduce effectiveness of such medications. Closely monitor for reduced effectiveness of medications that bind to the human neonatal Fc receptor. When concomitant long-term use of such medications is essential for patient care, consider discontinuing VYVGART HYTRULO and using alternative therapies.

8 USE IN SPECIFIC POPULATIONS

8.1 Pregnancy

Pregnancy Exposure Registry

There is a pregnancy exposure registry that monitors pregnancy outcomes in women exposed to VYVGART HYTRULO during pregnancy. Healthcare providers and patients may call 1-855-272-6524 or go to https://www.Vyvgartpregnancy.com to enroll in or to obtain information about the registry.

Risk Summary

There are no available data on the use of VYVGART HYTRULO or efgartigimod alfa containing products during pregnancy. There was no evidence of adverse developmental outcomes following the intravenous administration of efgartigimod alfa at up to 100 mg/kg/day in rats and rabbits (see Data).

The background rate of major birth defects and miscarriage in the indicated population is unknown. In the U.S. general population, the estimated background rate of major birth defects and miscarriage in clinically recognized pregnancies is 2% to 4% and 15% to 20%, respectively.

Clinical Considerations

Fetal/Neonatal Adverse Reactions

Monoclonal antibodies are increasingly transported across the placenta as pregnancy progresses, with the largest amount transferred during the third trimester. Therefore, efgartigimod alfa may be transmitted from the mother to the developing fetus.

As VYVGART HYTRULO is expected to reduce maternal IgG antibody levels, reduction in passive protection to the newborn is anticipated. Risk and benefits should be considered prior to administering live vaccines to infants exposed to VYVGART HYTRULO in utero [see Warnings and Precautions (5.1)].

Data

Animal Data

VYVGART HYTRULO for subcutaneous injection contains efgartigimod alfa and hyaluronidase [see Description (11)].

Efgartigimod alfa:

- Intravenous administration of efgartigimod alfa (0, 30, or 100 mg/kg/day) to pregnant rats and rabbits throughout organogenesis resulted in no adverse effects on embryofetal development in either species. Maternal efgartigimod alfa exposures at the highest no-effect doses were approximately 8 and 62 times, respectively, that in humans at the recommended human dose (RHD) of 1008 mg.
- Intravenous administration of efgartigimod alfa (0, 30, or 100 mg/kg/day) to rats throughout gestation and lactation resulted in no adverse effects on pre- or postnatal development. Maternal exposures at the highest no-effect dose were approximately 13 times that in humans at the RHD.

Hyaluronidase:

- In a study in which hyaluronidase (human recombinant) was administered by subcutaneous injection to pregnant mice throughout organogenesis, increased embryofetal mortality and decreased fetal body weights were observed at the highest doses tested. The no-effect dose for adverse effects on embryofetal development in the mouse was approximately 1800 times the dose of hyaluronidase at the recommended human dose (RHD) of VYVGART HYTRULO (1,008 mg efgartigimod alfa and 11,200 U hyaluronidase), on a U/kg basis.
- There were no adverse effects on pre- and postnatal development following subcutaneous administration of hyaluronidase (human recombinant) to mice throughout gestation and lactation at doses up to 5,000 times the dose of hyaluronidase at the RHD of VYVGART HYTRULO, on a U/kg basis.

8.2 Lactation

Risk Summary

There is no information regarding the presence of efgartigimod alfa or hyaluronidase, from administration of VYVGART HYTRULO, in human milk, the effects on the breastfed infant, or the effects on milk production. Maternal IgG is known to be present in human milk.

The developmental and health benefits of breastfeeding should be considered along with the mother's clinical need for VYVGART HYTRULO and any potential adverse effects on the breastfed infant from VYVGART HYTRULO or from the underlying maternal condition.

8.4 Pediatric Use

Safety and effectiveness in pediatric patients have not been established.

8.5 Geriatric Use

Clinical studies of VYVGART HYTRULO did not include sufficient numbers of patients aged 65 and older to determine whether they respond differently from younger adult patients.

8.6 Renal Impairment

No dose adjustment of VYVGART HYTRULO is needed for patients with mild renal impairment. There are insufficient data to evaluate the impact of moderate renal impairment (eGFR 30-59 mL/min/1.73 m^2) and severe renal impairment (eGFR <30 mL/min/1.73 m^2) on pharmacokinetic parameters of VYVGART HYTRULO [see Clinical Pharmacology (12.3)].

11 DESCRIPTION

VYVGART HYTRULO is a fixed-combination drug product containing efgartigimod alfa and hyaluronidase (human recombinant).

Efgartigimod alfa, a neonatal Fc receptor blocker, is a human immunoglobulin G1 (IgG1) -derived Fc fragment (fragment, crystallized) of the za allotype, produced in Chinese hamster ovary (CHO) cells. The efgartigimod alfa Fc fragment is a homodimer consisting of two identical peptide chains each consisting of 227 amino acids linked together by two interchain disulfide bonds with affinity for FcRn. The molecular weight of efgartigimod alfa is approximately 54 kDa.

Hyaluronidase (human recombinant) is an endoglycosidase used to increase the dispersion and absorption of co-administered drugs when administered subcutaneously. Hyaluronidase (human recombinant) is a glycosylated single-chain protein produced by Chinese hamster ovary cells containing a DNA plasmid encoding for a soluble fragment of human hyaluronidase (PH20). Hyaluronidase (human recombinant) has a molecular weight of approximately 61 kDa.

VYVGART HYTRULO (efgartigimod alfa and hyaluronidase-qvfc) injection is a sterile, preservative free, yellowish, clear to opalescent solution supplied in a single-dose prefilled syringe or vial for subcutaneous injection.

Each 5 mL single-dose prefilled syringe contains 1,000 mg of efgartigimod alfa and 10,000 units of hyaluronidase (human recombinant). Each mL contains 200 mg of efgartigimod alfa, 2,000 units of hyaluronidase (human recombinant) and arginine hydrochloride (10.5 mg), histidine (1.4 mg), L-histidine hydrochloride monohydrate (2.2 mg), methionine (1.5 mg), polysorbate 80 (0.4 mg), sodium chloride (4.1 mg), sucrose (20.5 mg), and Water for Injection, USP, at a pH of 6.0.

Each 5.6 mL single-dose vial contains 1,008 mg of efgartigimod alfa and 11,200 units of hyaluronidase (human recombinant). Each mL contains 180 mg of efgartigimod alfa, 2,000 units of hyaluronidase (human recombinant) and

- histidine (1.4 mg), L- histidine hydrochloride monohydrate (2.2 mg), methionine (1.5 mg), polysorbate 20 (0.4 mg), sodium chloride (5.8 mg), sucrose (20.5 mg), and Water for Injection, USP, at a pH of 6.0 or
- arginine hydrochloride (10.5 mg), histidine (1.4 mg), L- histidine hydrochloride monohydrate (2.2 mg), methionine (1.5 mg), polysorbate 80 (0.4 mg), sodium chloride (4.1 mg), sucrose (20.5 mg), and Water for Injection, USP, at a pH of 6.0.

12 CLINICAL PHARMACOLOGY

12.1 Mechanism of Action

VYVGART HYTRULO is a coformulation of efgartigimod alfa and hyaluronidase.

Efgartigimod alfa is a human IgG1 antibody fragment that binds to the neonatal Fc receptor (FcRn), resulting in the reduction of circulating IgG.

Hyaluronidase increases permeability of the subcutaneous tissue by depolymerizing hyaluronan. This effect is transient, and permeability of the subcutaneous tissue is restored within 24 to 48 hours.

12.2 Pharmacodynamics

In Study 1 [see Clinical Studies (14)], the pharmacological effect of efgartigimod alfa-fcab was assessed by measuring the decrease in serum IgG levels and AChR autoantibody levels. In patients testing positive for AChR antibodies and who were treated with efgartigimod alfa-fcab intravenous, there was a reduction in total IgG levels relative to baseline. Decrease in AChR autoantibody levels followed a similar pattern. A decrease in AChR-Ab was associated with a clinical response in AChR-Ab positive patients, as measured by the change from baseline in MG- ADL total score.

In Study 2, the pharmacological effect of VYVGART HYTRULO administered subcutaneously (SC) at 1,008 mg / 11,200 Units was compared to efgartigimod alfa-fcab administered intravenously at 10 mg/kg (EFG IV) in gMG patients. The maximum mean reduction in AChR-Ab level was observed at week 4, with a mean reduction of 62.2% and 59.7% in the VYVGART HYTRULO SC and efgartigimod alfa-fcab IV arm, respectively. The decrease in total IgG levels followed a similar pattern. The 90% confidence intervals for the geometric mean ratios of AChR-Ab reduction at day 29 and AUEC0-4w (area under the effect-time curve from time 0 to 4 weeks post dose) were within the range of 80% to 125%, indicating no clinically significant difference between the two formulations.

12.3 Pharmacokinetics

Efgartigimod alfa exposures were approximately dose-proportional up to the highest subcutaneously tested dose of VYVGART HYTRULO (1750 mg, 1.75 times the recommended dosage).

Absorption

The rate and extent of absorption from a single-dose prefilled syringe and single-dose vial are similar.

Distribution

The volume of distribution is 15 to 20L.

Metabolism and Elimination

Efgartigimod alfa and hyaluronidase are expected to be degraded by proteolytic enzymes into small peptides and amino acids.

The terminal half-life is 80 to 120 hours (3 to 5 days).

After a single intravenous dose of 10 mg/kg efgartigimod alfa-fcab in healthy subjects, less than 0.1% of the administered dose was recovered in urine.

Specific Populations

Age, Sex and Race

A population pharmacokinetics analysis assessing the effects of age, body weight, sex, and race did not suggest any clinically significant impact of these covariates on efgartigimod alfa exposures.

Body Weight

A population pharmacokinetics analysis suggests that the influence of body weight on efgartigimod alfa exposure after administration of VYVGART HYTRULO SC 1008 mg was limited and not clinically relevant.

Patients with Renal Impairment

No dedicated pharmacokinetic study has been performed in patients with renal impairment.

Population PK analyses of data from the VYVGART HYTRULO clinical studies indicated that patients with mild renal impairment (eGFR 60-89 mL/min/1.73 m^2) had 11 to 20% increase in exposure relative to the exposure in patients with normal renal function [see Use in Specific Populations (8.6)].

Patients with Hepatic Impairment

No dedicated pharmacokinetic study has been performed in patients with hepatic impairment. Hepatic impairment is not expected to affect the pharmacokinetics of efgartigimod alfa.

Drug Interaction Studies

Clinical drug interactions studies have not been performed with efgartigimod alfa.

P450 Enzymes

Efgartigimod alfa is not metabolized by cytochrome P450 enzymes; therefore, interactions with concomitant medications that are substrates, inducers, or inhibitors of cytochrome P450 enzymes are unlikely.

Drug Interactions with Other Drugs or Biological Products

Efgartigimod alfa may decrease concentrations of compounds that bind to the human FcRn [see Drug Interactions (7.1)].

12.6 Immunogenicity

The observed incidence of anti-drug antibodies is highly dependent on the sensitivity and specificity of the assay. Differences in assay methods preclude meaningful comparisons of the incidence of anti-drug antibodies in the studies described below with the incidence of anti-drug antibodies in other studies, including those of VYVGART HYTRULO or of other efgartigimod products.

In Study 2, in up to 10 weeks following the initiation of a treatment period with 4 weekly administrations, the incidence of anti-efgartigimod alfa antibodies was 35% (19/55) following treatment with VYVGART HYTRULO and 20% (11/55) in patients receiving intravenous efgartigimod alfa-fcab. For both IV and SC arms, neutralizing anti-efgartigimod alfa antibodies were detected in 4% (2/55) of patients.

In Study 3, in up to 12 weeks of treatment in stage A and 48 weeks in stage B, the incidence of anti-efgartigimod alfa antibodies was 6% (20/317) in stage A and 2% (2/111) in stage B, following treatment with VYVGART HYTRULO. Neutralizing anti-efgartigimod alfa antibodies were detected in 0.3% (1/317) of patients in stage A and in no patient in stage B.

Some neutralizing antibodies may not be detected by the assay. The available data are too limited to make definitive conclusions regarding immunogenicity and the effect on pharmacokinetics, safety, or efficacy of VYVGART HYTRULO.

13 NONCLINICAL TOXICOLOGY

13.1 Carcinogenesis, Mutagenesis, Impairment of Fertility

VYVGART HYTRULO for subcutaneous injection contains efgartigimod alfa and hyaluronidase [see Description (11)].

Carcinogenesis and Mutagenesis

No studies have been conducted to assess the carcinogenic potential of efgartigimod alfa.

No studies have been conducted to assess the genotoxic potential of efgartigimod alfa.

No carcinogenicity or genotoxicity studies were conducted for human recombinant hyaluronidase.

Impairment of Fertility

Intravenous administration of efgartigimod alfa (0, 30, or 100 mg/kg/day) to male and female rats prior to and during mating and continuing in females through gestation day 7 resulted in no adverse effects on fertility. Efgartigimod alfa exposures at the highest no-effect dose were approximately 12 times that in humans at the recommended human dose of 1008 mg. There were no effects on reproductive tissues in monkeys following subcutaneous administration of hyaluronidase (human recombinant) doses up to approximately 1,200 times the dose of hyaluronidase at the recommended human dose (RHD) of VYVGART HYTRULO (1,008 mg efgartigimod alfa and 11,200 U hyaluronidase) on a U/kg basis for 39 weeks. No systemic exposure to hyaluronidase was observed at doses up to approximately 120 times the dose of hyaluronidase at the RHD of VYVGART HYTRULO, on a U/kg basis.

14 CLINICAL STUDIES

14.1 Generalized Myasthenia Gravis

Study 1 (described below) which established the effectiveness of efgartigimod alfa-fcab for the treatment of generalized myasthenia gravis (gMG) in adults who are AChR antibody positive was conducted with efgartigimod alfa-fcab intravenous formulation. In Study 2, VYVGART HYTRULO demonstrated a comparable pharmacodynamic effect on AChR antibody reduction as compared to the efgartigimod alfa-fcab intravenous formulation, which established the efficacy of VYVGART HYTRULO [see Clinical Pharmacology (12.2)].

Study 1 (Efgartigimod Alfa-fcab Intravenous)

The efficacy of efgartigimod alfa-fcab intravenous (EFG IV) for the treatment of generalized myasthenia gravis (gMG) in adults who are AChR antibody positive was established in a 26-week, multicenter, randomized, double-blind, placebo-controlled trial (Study 1; NCT03669588).

Study 1 enrolled patients who met the following criteria at screening:

- Myasthenia Gravis Foundation of America (MGFA) clinical classification class II to IV
- MG-Activities of Daily Living (MG-ADL) total score of ≥ 5
- On stable dose of MG therapy prior to screening, that included acetylcholinesterase (AChE) inhibitors, steroids, or non-steroidal immunosuppressive therapies (NSISTs), either in combination or alone
- IgG levels of at least 6 g/L

A total of 167 patients were enrolled in Study 1 and were randomized to receive either EFG IV 10mg/kg (1200 mg for those weighing 120 kg or more) (n=84) or placebo (n=83). Baseline characteristics were similar between treatment groups. Patients had a median age of 46 years at screening (range: 19 to 81 years) and a median time since diagnosis of 7 years. Seventy-one percent were female, and 84% were White. Median MG-ADL total score was 9, and median Quantitative Myasthenia Gravis (QMG) total score was 16. The majority of patients (n=65 for EFG IV; n=64 for placebo) were positive for AChR antibodies.

At baseline, over 80% of patients in each group received AChE inhibitors, over 70% in each treatment group received steroids, and approximately 60% in each treatment group received NSISTs, at stable doses.

Patients were treated with 10 mg/kg EFG IV administered as an intravenous infusion over one hour once weekly for 4 weeks. In patients weighing 120 kg or more, EFG IV was administered as 1200 mg per infusion. Subsequent treatment cycles were administered based on clinical evaluation, but no sooner than 28 days from the last administration of the previous treatment cycle.

The efficacy of EFG IV was measured using the Myasthenia Gravis-Specific Activities of Daily Living scale (MG-ADL) which assesses the impact of gMG on daily functions of 8 signs or symptoms that are typically affected in gMG. Each item is assessed on a 4-point scale where a score of 0 represents normal function and a score of 3 represents loss of ability to perform that function. A total score ranges from 0 to 24, with the higher scores indicating more impairment. In this study, an MG-ADL responder was defined as a patient with a 2-point or greater reduction in the total MG-ADL score compared to the treatment cycle baseline for at least 4 consecutive weeks, with the first reduction occurring no later than 1 week after the last infusion of the cycle.

The primary efficacy endpoint was the comparison of the percentage of MG-ADL responders during the first treatment cycle between treatment groups in the AChR-Ab positive population. A statistically significant difference favoring EFG IV was observed in the MG-ADL responder rate during the first treatment cycle [67.7% in the EFG IV-treated group vs 29.7% in the placebo- treated group (p <0.0001)].

The efficacy of EFG IV was also measured using the Quantitative Myasthenia Gravis (QMG) total score which is a 13-item categorical grading system that assesses muscle weakness. Each item is assessed on a 4-point scale where a score of 0 represents no weakness and a score of 3 represents severe weakness. A total possible score ranges from 0 to 39, where higher scores indicate more severe impairment. In this study, a QMG responder was defined as a patient who had a 3-point or greater reduction in the total QMG score compared to the treatment cycle baseline for at least 4 consecutive weeks, with the first reduction occurring no later than 1 week after last infusion of the cycle.

The secondary endpoint was the comparison of the percentage of QMG responders during the first treatment cycle between both treatment groups in the AChR-Ab positive patients. A statistically significant difference favoring EFG IV was observed in the QMG responder rate during the first treatment cycle [63.1% in the EFG IV-treated group vs 14.1% in the placebo-treated group (p <0.0001)].

The results are presented in Table 2.

Table 2: MG-ADL and QMG Responders During Cycle 1 in AChR-Ab Positive Patients (mITT Analysis Set)
 | EFG IV n=65 % | Placebo n=64 % | P-value | Odds Ratio (95% CI)
MG-ADL Responders | 67.7 | 29.7 | < 0.0001 | 4.951 (2.213, 11.528)
QMG Responders | 63.1 | 14.1 | < 0.0001 | 10.842 (4.179, 31.200)
EFG IV= Efgartigimod alfa-fcab intravenous; MG-ADL=Myasthenia Gravis Activities of Daily Living; QMG =Quantitative Myasthenia Gravis; mITT=modified intent-to-treat; n=number of patients for whom the observation was reported; CI = confidence interval;
Logistic regression stratified for AChR-Ab status (if applicable), Japanese/Non-Japanese and standard of care, with baseline MG-ADL as covariate / QMG as covariates
Two-sided exact p-value

Figure 1 shows the mean change from baseline on the MG-ADL during cycle 1.

Figure 1: Mean Change in Total MG-ADL From Cycle 1 Baseline Over Time in AChR-Ab Positive Patients (mITT Analysis Set)

Figure 2 shows the distribution of response on the MG-ADL and QMG during cycle 1, four weeks after the first infusion with EFG IV.

Figure 2: Percentage of Patients with MG-ADL and QMG Total Score Change 4 Weeks Post Initial Infusion of the First Cycle in AChR-Ab Positive Patients

14.2 Chronic Inflammatory Demyelinating Polyneuropathy

The efficacy of VYVGART HYTRULO for the treatment of adults with chronic inflammatory demyelinating polyneuropathy (CIDP) was established in a two stage, multicenter study (Study 3; NCT04281472). Study 3 included a run-in period of up to 12 weeks after withdrawal of existing treatment for CIDP in order to identify patients with active disease, followed by an open-label period to identify VYVGART HYTRULO responders (stage A) who then entered a randomized, double-blind, placebo-controlled, withdrawal period (stage B).

Study 3 enrolled male and female patients age 18 years and older, who at the time of screening, had a documented diagnosis of definite or probable CIDP using the European Federation of Neurological Societies/Peripheral Nerve Society (EFNS/PNS; 2010) criteria for progressing or relapsing forms.

The Inflammatory Neuropathy Cause and Treatment disability score (INCAT) is a scale used to assess the impact of CIDP on daily upper and lower limb function, and is composed of the arm score and leg score (0 to 5 points for each). A total score on the INCAT ranges from 0 to 10 points with a higher number representing more disability. The adjusted INCAT (aINCAT) disability score, identical to the INCAT disability score but with changes in the upper limb function from 0 (normal) to 1 (minor symptoms) excluded, was used to assess efficacy for VYVGART HYTRULO for the treatment of CIDP.

Stage A

In stage A, a total of 322 patients received up to 12 once weekly subcutaneous injections of VYVGART HYTRULO 1008 mg / 11,200 units until evidence of improvement occurred at two consecutive study visits. Improvement was defined as aINCAT improvement ≥1 point, I-RODS improvement ≥4 points, or mean grip strength improvement ≥ 8 kPa. Stage A included 228 patients currently receiving standard-of-care therapy and 94 patients who had either not received prior treatment for CIDP or were not treated with standard-of-care therapy for at least 6 months before study entry. Sixty-nine percent of patients (n=221) who had documented improvement at two consecutive visits during Stage A then entered Stage B. A total of 36 patients (11%) who demonstrated lack of efficacy and 19 patients (6%) that had CIDP worsening as determined by reasonable clinical judgement of investigator, during Stage A did not enter Stage B.

Stage B

In stage B, a total of 221 patients were randomized to receive once weekly subcutaneous injections of VYVGART HYTRULO 1008 mg / 11,200 units (n=111) or placebo (n=110).

Baseline characteristics of patients in stage B were similar between treatment groups. Patients had a median age of 55 years (range: 20 to 82 years), a median time since CIDP diagnosis of 2.2 years, and median INCAT score of 3.0. Sixty-four percent were male and 65% were White, 30% Asian, and 1% African American.

Stage B included 146 patients currently receiving standard-of-care therapy and 75 patients who had either not received prior treatment for CIDP or were not treated with standard-of-care therapy for at least 6 months before study entry.

The primary endpoint was the time to clinical deterioration defined as a 1-point increase in aINCAT at two consecutive visits or a >1-point increase in aINCAT at one visit. Patients who had clinical deterioration or completed week 48 in Stage B without clinical deterioration were withdrawn from the placebo-controlled portion of the study. The study stopped when 88 events of clinical deterioration occurred for the primary endpoint analysis.

Patients who received VYVGART HYTRULO experienced a longer time to clinical deterioration (i.e., increase of ≥1 point in aINCAT score) compared to patients who received placebo, which was statistically significant, as demonstrated by a hazard ratio of 0.394 [95% CI (0.253; 0.614) p<0.0001]. The results are presented in Table 3 and Figure 3.

Table 3: Time to First Increase of ≥1 Point in aINCAT Score In Patients With CIDP In Study 3 Stage B
 | Stage B
 | VYVGART HYTRULO | Placebo
 | (N=111) | (N=110)
Time to 1st aINCAT increase (clinical deterioration) in days
Hazard ratio (95% CI) | 0.394 (0.253; 0.614) p-value <0.0001
N=number of patients in the analysis set; %: percentage; aINCAT: adjusted Inflammatory Neuropathy Cause and Treatment

Figure 3: Time To The First aINCAT Increase (Kaplan-Meier Curve) In Patients With CIDP In Study 3 Stage B

Note: The time to clinical deterioration is defined as the time in days from the first VYVGART HYTRULO or placebo administration in Stage B to the first occurrence of either: an increase in aINCAT score of 1 point compared with Stage B baseline if confirmed at the next visit or an increase in aINCAT score of >1 point compared with Stage B baseline.

16 HOW SUPPLIED/STORAGE AND HANDLING

VYVGART HYTRULO (efgartigimod alfa and hyaluronidase-qvfc) injection is a preservative free, sterile, yellowish, clear to opalescent solution supplied as a single-dose prefilled syringe or vial.

Single-Dose Prefilled Syringe

Each single-dose prefilled syringe contains 1,000 mg efgartigimod alfa and 10,000 units hyaluronidase per 5 mL (200 mg/2,000 units per mL). It is available in cartons of one or four single-dose prefilled syringes (NDC 73475-1221-1 or NDC 73475-1221-4). The safety needle that is 25G, 5/8 inches length, and thin wall type is not included in the carton.

Store VYVGART HYTRULO prefilled syringe refrigerated at 2°C to 8°C (36°F to 46°F) in the original carton to protect from light until time of use. Do not freeze. Do not shake.

If needed, prefilled syringes may be stored at room temperature at up to 30°C (86°F) in the original carton for a single period of up to 30 days after removing from refrigerator or until expiration date on the carton, whichever occurs first. Record the date removed from the refrigerator on the carton.

Single-Dose Vial

Each single-dose vial contains 1,008 mg efgartigimod alfa and 11,200 units hyaluronidase per 5.6 mL (180 mg/2,000 units per mL). It is available in carton of one single-dose vial (NDC 73475-3102-3).

STORAGE AND HANDLING

Store VYVGART HYTRULO vials refrigerated at 2°C to 8°C (36°F to 46°F) in the original carton to protect from light until time of use. Do not freeze. Do not shake.

If needed, unopened vials may be stored in the original carton for up to 3 days at room temperature at 20°C to 25°C (68°F to 77°F) for a single period before administration or returned to refrigeration. Do not store the vial at room temperature more than one time. Record the date removed from and the date returned to the refrigerator on the carton.

17 PATIENT COUNSELING INFORMATION

Advise the patient and/or caregiver to read FDA-approved patient labeling (Patient Information and Instructions for Use).

Infections

Instruct patients to communicate any history of infections to the healthcare provider and to contact their healthcare provider if they develop any symptoms of an infection. Advise patients to complete age-appropriate vaccines according to immunization guidelines prior to initiation of a new treatment cycle with VYVGART HYTRULO. Administration of live vaccines is not recommended during treatment with VYVGART HYTRULO [see Warnings and Precautions (5.1)].

Hypersensitivity Reactions

Inform patients that hypersensitivity reactions, including angioedema and anaphylaxis, have occurred in patients who were treated with efgartigimod alfa products. Inform patients about the signs and symptoms of these reactions, and advise patients to contact their healthcare provider immediately if these occur [see Warnings and Precautions (5.2)].

Infusion/injection-Related Reactions

Advise patients of the potential risk of infusion/injection-related reactions, which can include hypertension, chills, shivering, and chest, abdominal, and back pain [see Warnings and Precautions (5.3)].

Neurological Symptoms

Instruct patients to communicate any worsening of neurological symptoms to their prescriber. Symptom progression may indicate a lack of efficacy in these patients.

Instruction on Injection Technique

If a patient or caregiver is to administer subcutaneous VYVGART HYTRULO prefilled syringe, instruct them in proper injection technique (e.g., site selection and duration of injection) [see Instructions for Use].

Pregnancy Registry

There is a pregnancy exposure registry that monitors pregnancy outcomes in women exposed to VYVGART HYTRULO during pregnancy. Encourage participation and advise patients about how they may enroll in the registry [see Use in Specific Populations (8.1)].

Manufactured by:

argenx BV
Industriepark 7
9052 Zwijnaarde, Belgium
U.S. License No. 2217

Halozyme, Inc.
12390 El Camino Real
San Diego, CA 92130
U.S. License No. 2187

Distributed by:

argenx US, Inc.
33 Arch Street
Boston, MA 02110

VYVGART HYTRULO is a registered trademark of argenx BV.
© 2026 argenx BV

For patent information: www.argenx.com/patents

PATIENT INFORMATION
VYVGART HYTRULO® [viv' gart hye troo' loe]
(efgartigimod alfa and hyaluronidase-qvfc)
injection, for subcutaneous use

What is VYVGART HYTRULO?
VYVGART HYTRULO is a prescription medicine used to treat adults with:

- generalized myasthenia gravis (gMG) who are anti-acetylcholine receptor (AChR) antibody positive.
- chronic inflammatory demyelinating polyneuropathy (CIDP).

It is not known if VYVGART HYTRULO is safe and effective in children.

Do not take VYVGART HYTRULO if you:

- are allergic to efgartigimod alfa, hyaluronidase, or any of the ingredients in VYVGART HYTRULO. See the end of this leaflet for a complete list of ingredients in VYVGART HYTRULO. VYVGART HYTRULO can cause serious allergic reactions and a decrease in blood pressure leading to fainting.

Before taking VYVGART HYTRULO, tell your healthcare provider about all of your medical conditions, including if you:

- have an infection or fever.
- have recently received or are scheduled to receive any vaccinations.
- have any history of allergic reactions.
- have kidney (renal) problems.
- are pregnant or plan to become pregnant. It is not known whether VYVGART HYTRULO will harm your unborn baby.
  - Pregnancy Exposure Registry. There is a pregnancy exposure registry for women who use VYVGART HYTRULO during pregnancy. The purpose of this registry is to collect information about your health and your baby. Your healthcare provider can enroll you in this registry. You may also enroll yourself or get more information about the registry by calling 1-855-272-6524 or going to https://www.Vyvgartpregnancy.com
- are breastfeeding or plan to breastfeed. It is not known if VYVGART HYTRULO passes into your breast milk.

Tell your healthcare provider about all the medicines you take, including prescription and over-the-counter medicines, vitamins, and herbal supplements.

How should I take VYVGART HYTRULO?

- Take VYVGART HYTRULO exactly as your healthcare provider tells you to take it.
- VYVGART HYTRULO is injected under your skin (subcutaneously) only. Do not inject into a vein (intravenously).
- For gMG, VYVGART HYTRULO is injected 1 time weekly for 4 weeks (treatment cycle).Your healthcare provider will tell you when to administer your future treatment cycles.
- For CIDP, VYVGART HYTRULO is injected 1 time weekly.
- VYVGART HYTRULO comes in a single-dose prefilled syringe and single-dose vial.
- Only a healthcare provider should inject VYVGART HYTRULO using the single-dose vial.
- If you are prescribed the VYVGART HYTRULO prefilled syringe, you or your caregiver should receive training on the right way to prepare and inject VYVGART HYTRULO prefilled syringe.
- Do not try to inject VYVGART HYTRULO prefilled syringe until you have been shown the right way by a healthcare provider. See the detailed Instructions for Use that comes with VYVGART HYTRULO prefilled syringe.
- Monitor for signs and symptoms of an allergic reaction for at least 30 minutes after administration. See "What are the possible side effects of VYVGART HYTRULO?"
- If you miss a dose of VYVGART HYTRULO, you may give the injection for up to 3 days after the missed dose. After that, continue with the normal time between doses (dosing schedule).

What are the possible side effects of VYVGART HYTRULO?
VYVGART HYTRULO can cause side effects which can be serious, including:

- Infection. VYVGART HYTRULO may increase the risk of infection. If you have an active infection, your healthcare provider should delay your treatment with VYVGART HYTRULO until your infection is gone. Tell your healthcare provider right away if you get any of the following signs and symptoms of an infection:

- fever
- chills
- frequent and painful urination
- cough

- pain and blockage of nasal passages
- wheezing
- shortness of breath

- sore throat
- excess phlegm
- nasal discharge

- Allergic reactions (hypersensitivity reactions). VYVGART HYTRULO can cause allergic reactions that can be severe. These reactions can happen during, shortly after, or weeks after your VYVGART HYTRULO injection. Tell your healthcare provider or get emergency help right away if you have any of the following symptoms of an allergic reaction:

- rash
- swelling of the face, lips, throat, or tongue
- shortness of breath
- hives

- trouble breathing
- low blood pressure
- fainting

- Infusion or injection-related reactions. VYVGART HYTRULO can cause infusion or injection-related reactions. These reactions can happen during or shortly after your VYVGART HYTRULO injection. Tell your healthcare provider if you have any of the following symptoms of an infusion or injection-related reaction:

- high blood pressure
- chills

- shivering
- chest, stomach, or back pain

The most common side effects of VYVGART HYTRULO include:

- respiratory tract infection
- injection site reactions

- headache

- urinary tract infection

These are not all the possible side effects of VYVGART HYTRULO. Call your doctor for medical advice about side effects. You may report side effects to FDA at 1-800-FDA-1088.

How should I store VYVGART HYTRULO?
Refrigerated

- Store VYVGART HYTRULO in the refrigerator between 36°F to 46°F (2°C to 8°C).
- Only warm VYVGART HYTRULO by letting it sit on a flat surface for at least 30 minutes for the prefilled syringe and 15 minutes for the vial. Do not warm VYVGART HYTRULO any other way (e.g., with an external heat source).
- Store VYVGART HYTRULO in the original carton to protect from light until you are ready to use it.
- Do not freeze VYVGART HYTRULO.
- Do not shake VYVGART HYTRULO.
- Do not use VYVGART HYTRULO past the expiration date.
- VYVGART HYTRULO is for one-time use only (single-dose).
- Remove from the refrigerator only the dose you are preparing to inject. Future doses should remain refrigerated until ready to use.

Room temperature

- If needed, VYVGART HYTRULO may be stored at room temperature. Record the date you removed VYVGART HYTRULO from the refrigerator.

- Single-dose prefilled syringe may be stored at room temperature (up to 86°F (30°C)) for up to 30 days. When removed from the refrigerator and brought to room temperature VYVGART HYTRULO must be used within 30 days or thrown away.

- Single-dose vial may be stored at room temperature (between 68°F to 77°F (20°C to 25°C)) for up to 3 days. When removed from the refrigerator and brought to room temperature, VYVGART HYTRULO must be used within 3 days or thrown away.

- Do not put VYVGART HYTRULO back into the refrigerator after it has warmed to room temperature.

Keep VYVGART HYTRULO and all medicines out of the reach of children.

General information about the safe and effective use of VYVGART HYTRULO.
Medicines are sometimes prescribed for purposes other than those listed in a Patient Information leaflet. Do not use VYVGART HYTRULO for a condition for which it was not prescribed. Do not give VYVGART HYTRULO to other people, even if they have the same symptoms that you have. It may harm them. You can ask your pharmacist or healthcare provider for information about VYVGART HYTRULO that is written for health professionals.

What are the ingredients in VYVGART HYTRULO?
Active ingredients: efgartigimod alfa and hyaluronidase (human recombinant)
Inactive ingredients:

- single-dose prefilled syringe: arginine hydrochloride, histidine, L-histidine hydrochloride monohydrate, methionine, polysorbate 80, sodium chloride, sucrose, and water for injection, USP
- single-dose vial:
  - histidine, L-histidine hydrochloride monohydrate, methionine, polysorbate 20, sodium chloride, sucrose and water for injection, USP or
  - arginine hydrochloride, histidine, L- histidine hydrochloride monohydrate, methionine, polysorbate 80, sodium chloride, sucrose, and water for injection, USP.

Manufactured by:

- argenx BV Industriepark 7, 9052 Zwijnaarde, Belgium, U.S. License No. 2217
- Halozyme, Inc. 12390 El Camino Real, San Diego, CA 92130, U.S. License No. 2187

Distributed by: argenx US, Inc. 33 Arch Street, Boston, MA 02110
VYVGART HYTRULO is a registered trademark of argenx BV.
© 2026 argenx BV

This Patient Information has been approved by the U.S. Food and Drug Administration

Revised: 2/2026

INSTRUCTIONS FOR USE

VYVGART HYTRULO [viv' gart hye troo' loe]
(efgartigimod alfa and hyaluronidase-qvfc)
injection, for subcutaneous use
1,000 mg and 10,000 units/5 mL

This Instructions for Use contains information on how to inject VYVGART HYTRULO.

Important Information You Need to Know Before Injecting VYVGART HYTRULO

- VYVGART HYTRULO is for under the skin (subcutaneous) injection only.
- Be sure to read and understand this Instructions for Use before injecting VYVGART HYTRULO. Your healthcare provider should show you or your caregiver how to prepare and inject VYVGART HYTRULO the correct way before using it for the first time. Ask your healthcare provider if you have any questions.
- The prefilled syringe is for one-time-use only and cannot be reused.
- Do not use VYVGART HYTRULO if it has been at room temperature for longer than 30 days.
- Do not use the prefilled syringe if it is expired.
- Do not use the prefilled syringe if it is cracked, broken, or damaged. Return damaged prefilled syringes to the specialty pharmacy.
- Do not use a prefilled syringe if the liquid medicine is discolored or contains particles. The liquid medicine should look clear to yellowish in color. A little cloudiness is normal.
- Do not shake the prefilled syringe.
- You will need supplies that are not provided with VYVGART HYTRULO (see Figure J).

Storing VYVGART HYTRULO Prefilled Syringe

- Store VYVGART HYTRULO in the refrigerator between 36°F to 46°F (2°C to 8°C) (see Figure A).
- Keep the prefilled syringes in the original carton to protect them from light until ready to use.
- Keep VYVGART HYTRULO and all medicines out of the reach of children.

Do not freeze the prefilled syringes or store them in direct sunlight.
Do not use a prefilled syringe that has been frozen or left in direct sunlight.

Prefilled Syringe Parts

Safety Needle (not provided with VYVGART HYTRULO prefilled syringe) that is 25G, 5/8 inch length, thin wall

Gather and Check the Prefilled Syringe

1 Remove the carton from the refrigerator

1.1 Remove the carton containing the prefilled syringe from the refrigerator (see Figure C).

1.2 Remove 1 prefilled syringe from the carton (see Figure D) and place any remaining prefilled syringes back into the refrigerator for later use.

1.3 Remove the prefilled syringe from the tray (see Figure E).

2 Check the prefilled syringe before use

2.1 Check the expiration date on the prefilled syringe label (see Figure F).

Do not use the prefilled syringe if the expiration date has passed.

2.2 Check the condition of the prefilled syringe and the prefilled syringe cap (see Figure G).

Do not use the prefilled syringe if it is cracked, broken, damaged, or if the prefilled syringe cap is missing.

2.3 Check the appearance of the liquid medicine in the prefilled syringe (see Figure H).
The liquid medicine should look clear to yellowish in color. A little cloudiness is normal.

Do not use the prefilled syringe if the liquid medicine is discolored or contains particles.

Prepare for the Injection

3 Allow the prefilled syringe to warm to room temperature

3.1 Place the prefilled syringe on a clean flat surface and let it sit for at least 30 minutes, to allow it to warm to room temperature (see Figure I).

Do not attempt to warm the prefilled syringe in any other way.
Do not use the VYVGART HYTRULO prefilled syringe if it has been at room temperature for longer than 30 days.

4 Gather supplies and wash your hands

4.1 Gather the following supplies that are not provided with the prefilled syringe (see Figure J).

4.2 Wash your hands with soap and water (see Figure K).

5 Snap off the prefilled syringe cap and attach the safety needle

5.1 Carefully open the safety needle package and remove the needle (see Figure L).
Throw away the packaging into household trash.

5.2 Bend the prefilled syringe cap to one side to snap it off and remove it from the prefilled syringe (see Figure M).
Throw away the prefilled syringe cap into the household trash.

Do not touch the tip of the prefilled syringe after the prefilled syringe cap has been removed.

5.3 Hold the prefilled syringe by the syringe body in one hand, and attach the safety needle to the prefilled syringe by twisting it to the right (clockwise) until you feel resistance (see Figure N).

The safety needle is now attached to the prefilled syringe (see Figure O).

6 Choose and clean the injection site on the stomach (abdomen)

6.1 Choose an injection site on the stomach (abdomen) at least 2 inches away from the belly button (navel) (see Figure P).
Change (rotate) the injection site the next time you inject VYVGART HYTRULO.

Do not inject into skin that is irritated, red, bruised, infected, or tender. Do not inject into skin that is hard, scarred, or has moles.
Do not inject into a vein. VYVGART HYTRULO is for under the skin (subcutaneous) injection only.

6.2 Clean the chosen injection site with an alcohol swab and let it air dry (see Figure Q).

Do not blow on or touch the injection site after it has been cleaned.

Inject VYVGART HYTRULO

7 Pull back the needle shield and remove the clear needle cap

7.1 Pull the needle shield back (see Figure R).
Note: The needle shield will be used after the injection to cover the needle and protect from needle-stick injuries.

7.2 Hold the prefilled syringe body and remove the clear needle cap by pulling it straight off of the needle (see Figure S).
Throw away the clear needle cap into the household trash.

Do not recap the needle.

8 Give the injection

8.1 Pinch the cleaned injection site (Figure T).

While pinching the skin, insert the needle at a 45 to 90 degree angle all the way into the pinched skin (see Figure U).
Then release the pinched skin.

Do not pinch the skin too tightly as this can cause bruising.

8.2 Slowly press the thumb pad down all the way until it stops to inject the liquid medicine (see Figure V).
It will take about 20 to 30 seconds to inject all of the liquid medicine.
You will feel resistance as you press down. Inject more slowly in case there is discomfort.
It is ok if you need to pause or change your grip during the injection.

Do not try to force the thumb pad down quickly as this will make the thumb pad harder to press.

8.3 After all the liquid medicine is injected, remove the needle from the skin by pulling it straight out without changing the angle that it was inserted (see Figure W).

Throw away (dispose of) the Used Prefilled Syringe

9 Cover the needle and throw away the used prefilled syringe

9.1 Carefully push the needle shield over the needle until it snaps into place and covers the needle (see Figure X).
This helps to prevent needle-stick injuries.

Do not recap the needle using the clear needle cap. Only use the needle shield to cover the needle.

9.2 Throw away the used prefilled syringe, with the needle still attached, into an FDA-cleared sharps disposal container right away after use (see Figure Y).

Do not throw away (dispose of) loose needles and syringes in your household trash.

10 Treat the injection site

10.1 If there is a small amount of blood or liquid at the injection site, press a sterile gauze over the injection site until the bleeding stops (see Figure Z).
If needed, you may apply a small adhesive bandage.

Additional Disposal Information

If you do not have an FDA-cleared sharps disposal container, you may use a household container that is:

- made of a heavy-duty plastic,
- can be closed with a tight-fitting, puncture-resistant lid without sharps being able to come out,
- upright and stable during use,
- leak-resistant, and
- properly labeled to warn of hazardous waste inside the container.

When your sharps disposal container is almost full, you will need to follow your community guidelines for the right way to dispose of your sharps disposal container. There may be state or local laws about how you should throw away used needles and syringes.
For more information about safe sharps disposal, and for specific information about sharps disposal in the state that you live in, go to the FDA's website at: http://www.fda.gov/safesharpsdisposal.
Do not dispose of your used sharps disposal container in your household trash unless your community guidelines permit this. Do not recycle your used sharps disposal container.
Always keep the sharps disposal container out of the reach of children.

Additional Information

For more information, go to www.vyvgart.com or call 1-833-898-4278.
Manufactured by:
argenx BV
Industriepark 7
9052 Zwijnaarde, Belgium
U.S. License No. 2217
Halozyme, Inc.
12390 El Camino Real
San Diego, CA 92130
U.S. License No. 2187
Distributed by:
argenx US, Inc.
33 Arch Street
Boston, MA 02110

This Instructions for Use has been approved by the U.S. Food and Drug Administration

Issued: 4/2025

PRINCIPAL DISPLAY PANEL - 5.6 mL Vial Carton

NDC 73475-3102-3

VYVGART® Hytrulo
(efgartigimod alfa and
hyaluronidase-qvfc)

INJECTION

1,008 mg and 11,200 units/5.6 mL
(180 mg and 2,000 units/mL)

For subcutaneous injection
over 30 to 90 seconds

One single-dose vial

Discard unused portion

Must be administered by
a healthcare provider

Rx only

PRINCIPAL DISPLAY PANEL - 1,008 mg and 11,2000 units/5.6 mL Vial Carton

NDC 73475-3102-3

VYVGART® Hytrulo
(efgartigimod alfa and
hyaluronidase-qvfc)

INJECTION

1,008 mg and 11,200 units/5.6 mL
(180 mg and 2,000 units/mL)

For subcutaneous injection
over 30 to 90 seconds

One single-dose vial
Discard unused portion
Must be administered by
a healthcare provider

Rx only

PRINCIPAL DISPLAY PANEL - 5 mL Syringe Carton

NDC 73475-1221-1

VYVGART Hytrulo®
(efgartigimod alfa and hyaluronidase-qvfc)

INJECTION

1,000 mg and 10,000 units/5 mL
(200 mg and 2,000 units/mL)

For subcutaneous injection over 20 to 30 seconds

One single-dose prefilled syringe

Rx only